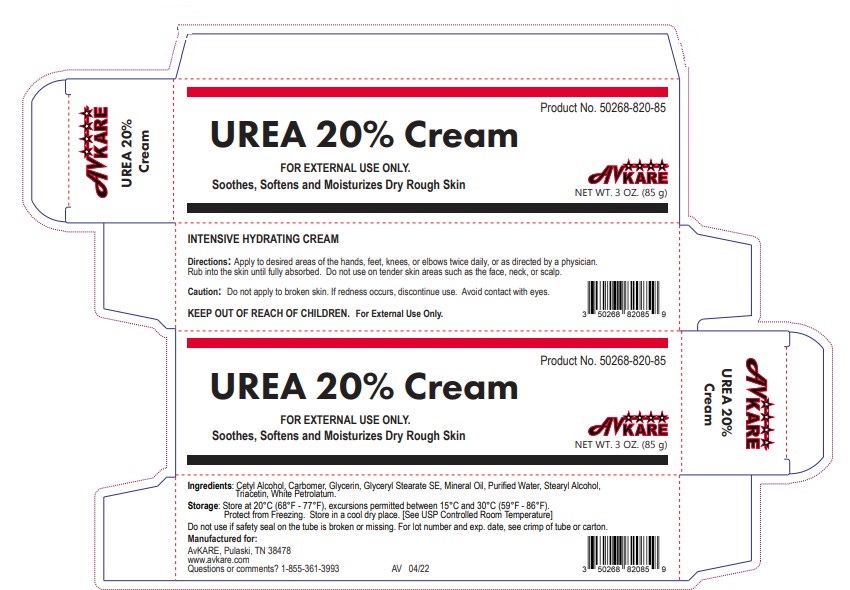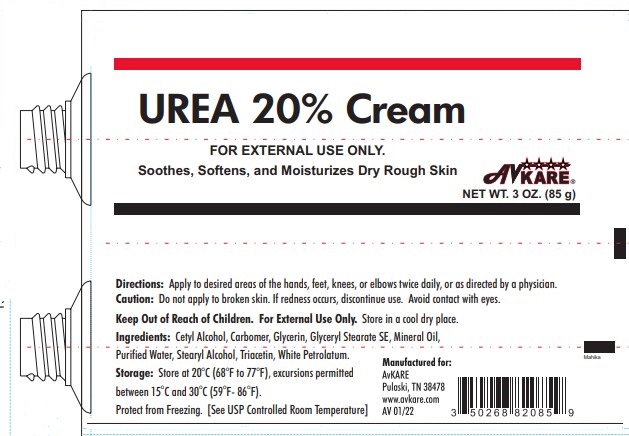 DRUG LABEL: Urea 20
NDC: 50268-820 | Form: GEL
Manufacturer: AvPAK
Category: otc | Type: HUMAN OTC DRUG LABEL
Date: 20260112

ACTIVE INGREDIENTS: UREA 200 mg/1 g
INACTIVE INGREDIENTS: CARBOMER HOMOPOLYMER, UNSPECIFIED TYPE; CETYL ALCOHOL; GLYCERIN; GLYCERYL STEARATE SE; MINERAL OIL; WATER; STEARYL ALCOHOL; TRIACETIN; WHITE PETROLATUM

Urea 20% Cream

Active Ingredient: UREA 20%

Purpose: Moisturizer

Usage: Soothes, Softens and Moisturizes Dry Rough Skin.

WARNINGS SECTION

Caution: Do not apply to broken skin. If redness occurs, discontinue use. Avoid contact with eyes.

KEEP OUT OF REACH OF CHILDREN. For External Use Only.

Do not use: Do not use if safety seal on the tube is broken or missing. For lot number and exp. date, see crimp of tube or carton.

WHEN USING

Directions: Apply to desired areas of the hands, feet, knees, or elbows twice daily, or as directed by a physician. Rub into the skin until fully absorbed. Do not use on tender skin areas such as the face, neck, or scalp.

Stop use: Do not apply to broken skin. If redness occurs, discontinue use. Avoid contact with eyes.

INACTIVE INGREDIENT

Inactive Ingredients: Cetyl Alcohol, Carbomer, Glycerin, Glyceryl Stearate SE, Mineral Oil, Purified Water, Stearyl Alcohol, Triacetin, White Petrolatum.

STORAGE AND HANDLING

Storage: Store at 20°C (68°F - 77°F), excursions permitted between 15°C and 30°C (59°F - 86°F). Protect from Freezing. Store in a cool dry place. [See USP Controlled Room Temperature]

Questions or comments? 1-855-361-3993

PACKAGE LABEL.PRINCIPAL DISPLAY PANEL

UREA 20% Cream
FOR EXTERNAL USE ONLY.
Soothes, Softens and Moisturizes Dry Rough Skin
AvKARE
NET WT. 3 OZ. (85 g)
Manufactured for: AvKARE,
Pulaski, TN 38478
www.avkare.com
Questions or comments? 1-855-361-3993 AV 04/22

UREA 20% Cream
Product No. 50268-820-85
FOR EXTERNAL USE ONLY.
Soothes, Softens and Moisturizes Dry Rough Skin
AvKARE
NET WT. 3 OZ. (85 g)